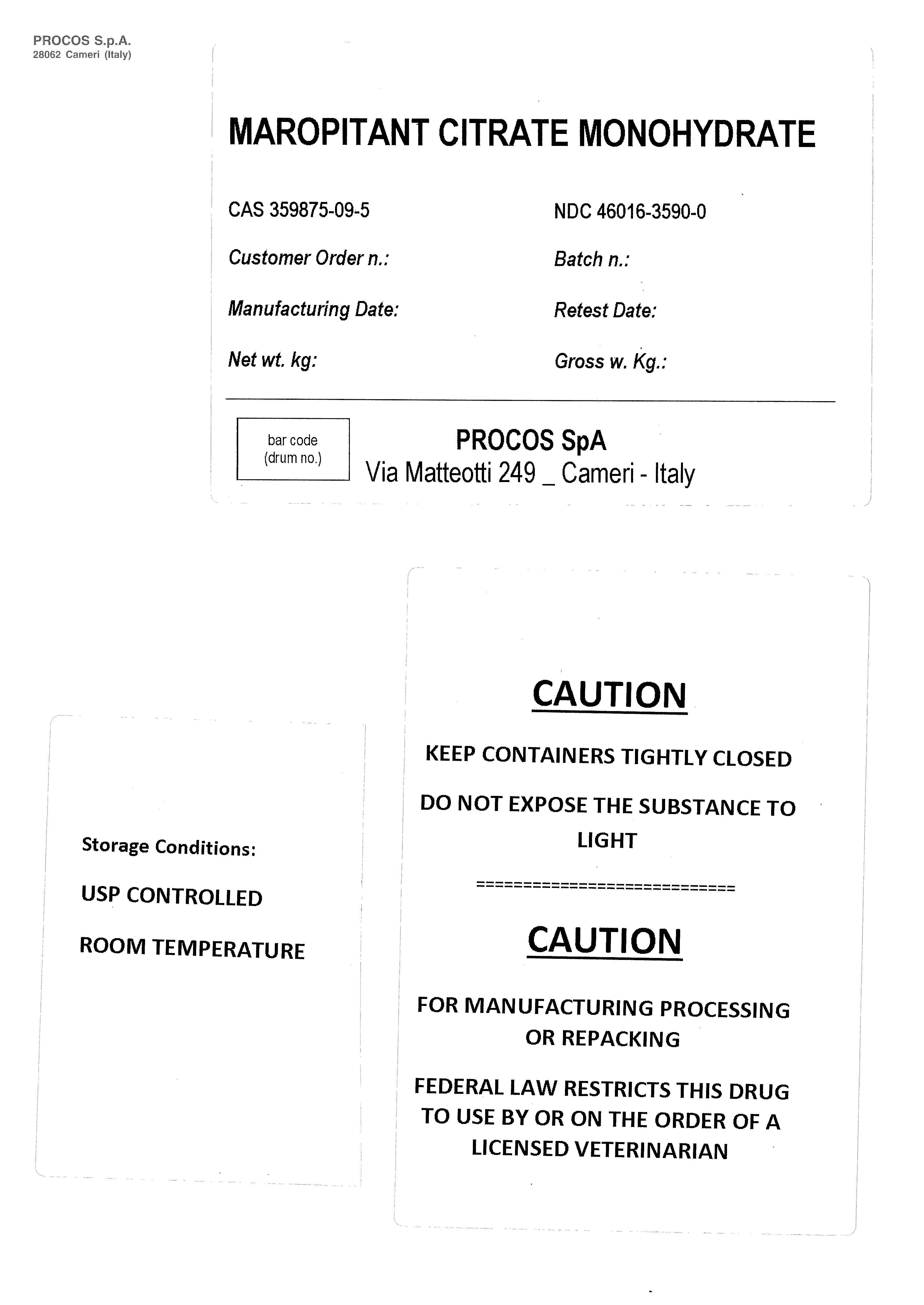 DRUG LABEL: MAROPITANT CITRATE MONOHYDRATE
NDC: 46016-3590 | Form: POWDER
Manufacturer: PROCOS SpA
Category: other | Type: BULK INGREDIENT - ANIMAL DRUG
Date: 20211022

ACTIVE INGREDIENTS: MAROPITANT CITRATE 50 kg/50 kg

MAROPITANT CITRATE MONOHYDRATE

MAROPITANT CITRATE MONOHYDRATE

CAS 359875-09-5 NDC 46016-3590-0

Customer Order n.: Batch n:

Manufacturing Date: Retest Date:

Net wt. kg: Gross w. Kg:

CAUTION

KEEP CONTAINERS TIGHTLY CLOSED. DO NOT EXPOSE THE SUBSTANCE TO LIGHT

CAUTION

FOR MANUFACTURING PROCESSING OR REPACKING

FEDERAL LAW RESTRICTS THIS DRUG TO USE BY OR ON THE ORDER OF A LICENSED VETERINARIAN

Storage Conditions:

USP CONTROLLED

ROOM TEMPERATURE